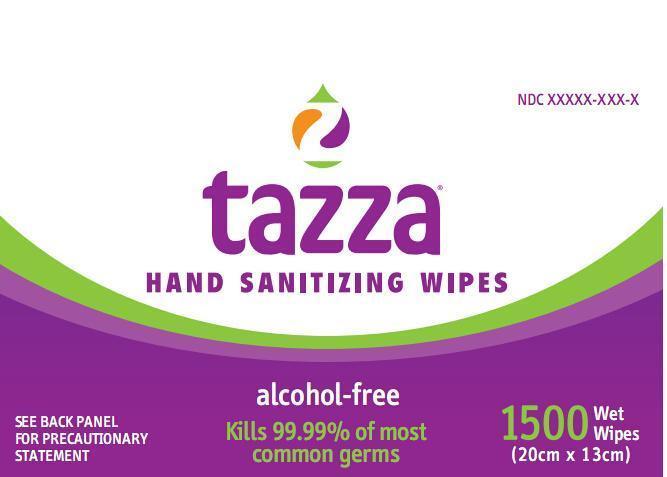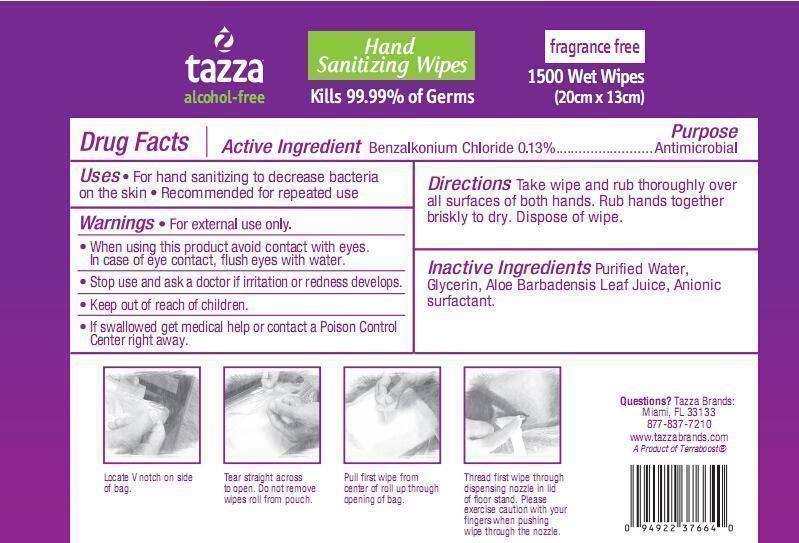 DRUG LABEL: Hand Sanitizing wipes
NDC: 61312-002 | Form: SWAB
Manufacturer: HANGZHOU GUOGUANG TOURING COMMODITY CO., LTD.
Category: otc | Type: HUMAN OTC DRUG LABEL
Date: 20180109

ACTIVE INGREDIENTS: BENZALKONIUM CHLORIDE 0.13 g/100 g
INACTIVE INGREDIENTS: GLYCERIN; ALOE VERA LEAF; SODIUM DODECYLBENZENESULFONATE; WATER

61312002

Active ingredient

Benzalkonium chloride 0.13%

Purpose

Antibacterial

Use

For hand sanitizing to decrease bacteria on the skin

recommended for repeated use

Warnings

For external use only.
When useing this product avoid contact with eyes.In case of eye contact,flush eyes with water.
Stop use and ask a doctor if irritation or redness develops.
Keep out of reach of children.
If swallowed, get medical help or contact a Poison Control Center right away.

Keep out of reach of children

if swallowed
get medical help or contact a Poison Control Center right away.

Directions

Take wipe and rub thoroughly over all surfaces of both hands,Rub hands together briskly to dry .Dispose of wipe.

INACTIVE INGREDIENT

Purified Water ,Glycerin,Aloe Barbadensis Leaf Juice,Anionic surfactant.